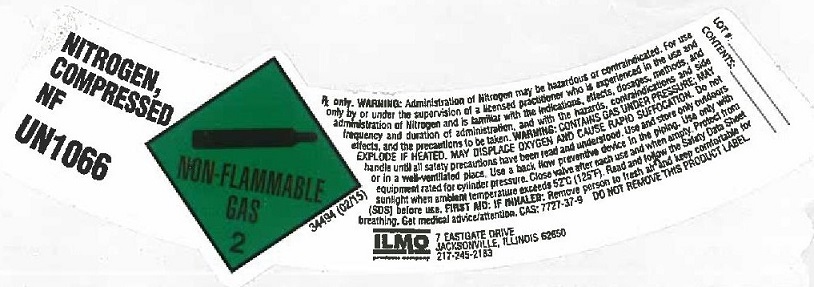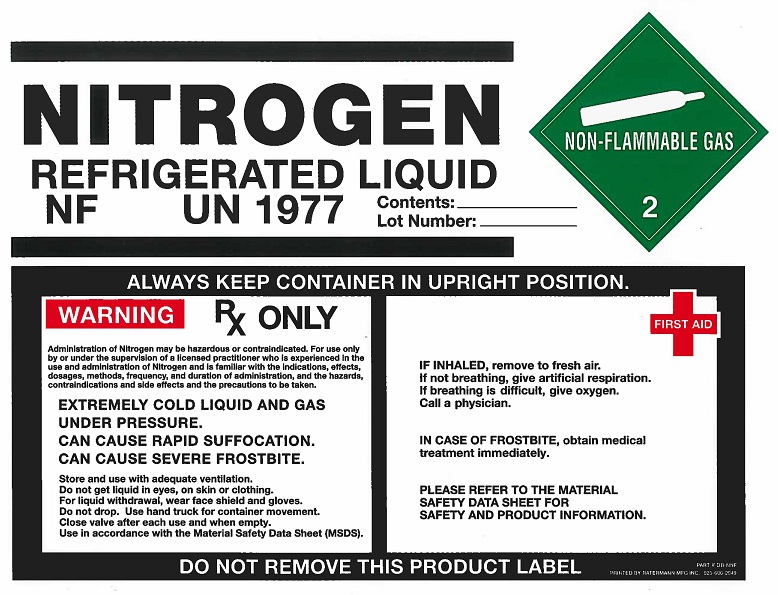 DRUG LABEL: Nitrogen
NDC: 51486-002 | Form: GAS
Manufacturer: ILMO Products Company
Category: prescription | Type: HUMAN PRESCRIPTION DRUG LABEL
Date: 20251029

ACTIVE INGREDIENTS: NITROGEN 990 mL/1 L

Nitrogen

PACKAGE LABEL

NITROGEN, COMPRESSED NF UN1066 NON-FLAMMABLE GAS 2
Rx only. WARNING: Administration of Nitrogen may be hazardous or contraindicated. For use only by or under the supervision of a licensed practitioner who is experienced in the use and administration of Nitrogen and is familiar with the indications, effects, dosages, methods, and frequency and duration of administration, and with the hazards, contraindications, and side effects and the precautions to be taken. WARNING: CONTAINS GAS UNDER PRESSURE; MAY EXPLODE IF HEATED. MAY DISPLACE OXYGEN AND CAUSE RAPID SUFFOCATION. Do not handle until all safety precautions have been read and understood. Use and store only outdoors or in a well-ventilated place. Use a back flow preventive device in the piping. Use only with equipment rated for cylinder pressure. Close valve after each use and when empty. Protect from sunlight when ambient temperature exceeds 52 degrees C (125 degrees F). Read and follow the Safety Data Sheet (SDS) before use. FIRST AID: IF INHALED: Remove person to fresh air and keep comfortable for breathing. Get medical advice/attention.
CAS: 7727-37-9 DO NOT REMOVE THIS PRODUCT LABEL.
LOT #: CONTENTS:
ILMO 7 EASTGATE DRIVE JACKSONVILLE, ILLINOIS 62650 217-245-2183

PACKAGE LABEL

NITROGEN REFRIGERATED LIQUID NF UN1977 Contents: Lot Number:
NON-FLAMMABLE GAS 2
ALWAYS KEEP CONTAINER IN UPRIGHT POSITION.
WARNING Rx ONLY Administration of Nitrogen may be hazardous or contraindicated. For use only by or under the supervision of a licensed practitioner who is experienced in the use and administration of Nitrogen and is familiar with the indications, effects, dosages, methods, and frequency and duration of administration, and with the hazards, contraindications, and side effects and the precautions to be taken.
EXTREMELY COLD LIQUID AND GAS UNDER PRESSURE. CAN CAUSE RAPID SUFFOCATION. CAN CAUSE SEVERE FROSTBITE.
Store and use with adequate ventilation. Do not get liquid in eyes, on skin or clothing. For liquid withdrawal, wear face shield and gloves. Do not drop. Use hand truck for container movement. Close valve after each use and when empty. Use in accordance with the material Safety Data Sheet (MSDS).
FIRST AID: IF INHALED, remove to fresh air. If not breathing , give artificial respiration. If breathing is difficult, give oxygen. Call a physician. IN CASE OF FROSTBITE, obtain medical treatment immediately. PLEASE REFER TO THE MATERIAL SAFETY DATA SHEET FOR SAGETY AND PRODUCT INFORMATION.
DO NOT REMOVE THIS PRODUCT LABEL